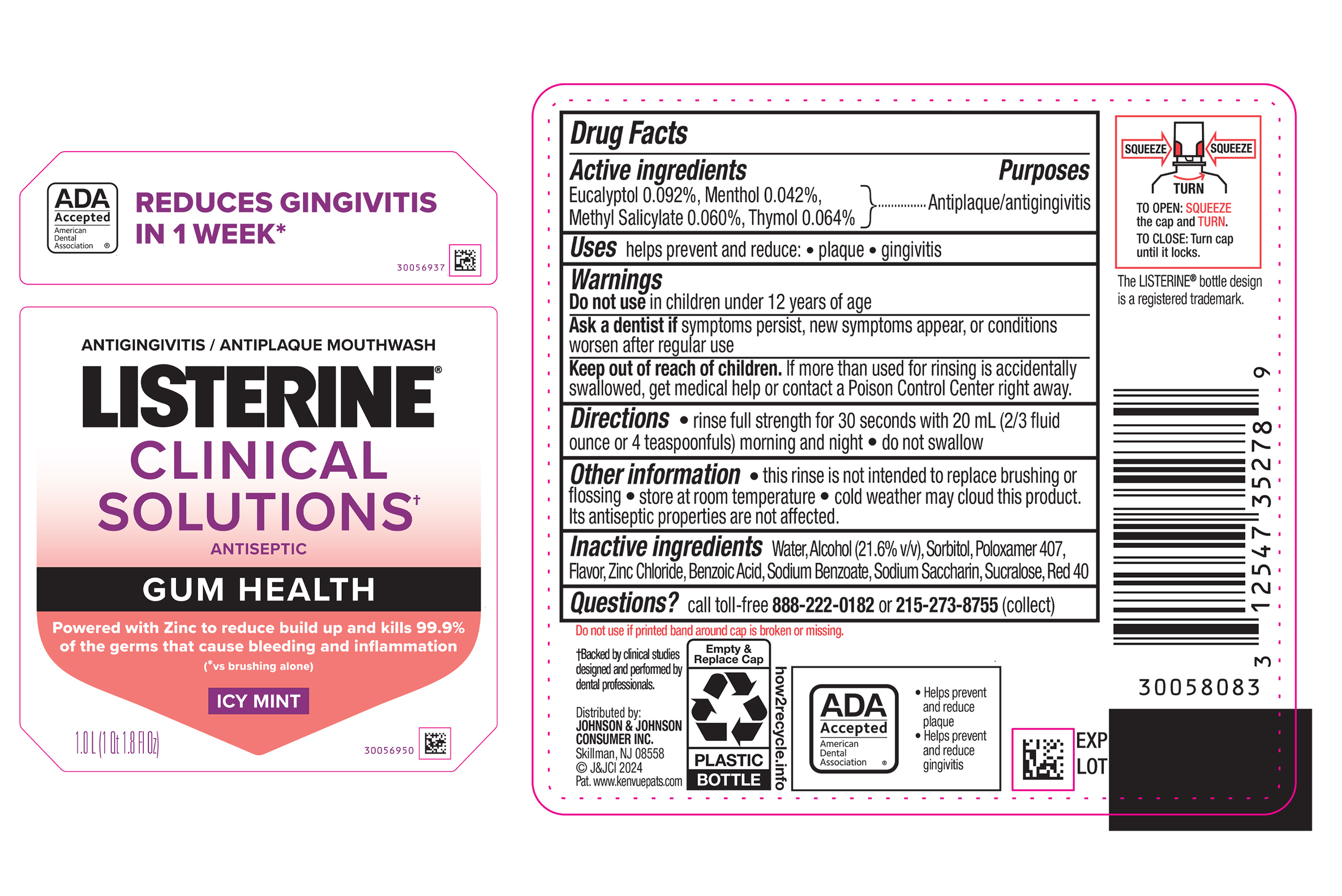 DRUG LABEL: Listerine Clinical Solutions Gum Health Icy Mint
NDC: 69968-0818 | Form: MOUTHWASH
Manufacturer: Kenvue Brands LLC
Category: otc | Type: HUMAN OTC DRUG LABEL
Date: 20250422

ACTIVE INGREDIENTS: EUCALYPTOL 0.92 mg/1 mL; MENTHOL 0.42 mg/1 mL; THYMOL 0.64 mg/1 mL; METHYL SALICYLATE 0.6 mg/1 mL
INACTIVE INGREDIENTS: WATER; ALCOHOL; SORBITOL; POLOXAMER 407; BENZOIC ACID; ZINC CHLORIDE; SODIUM BENZOATE; SUCRALOSE; SACCHARIN SODIUM; FD&C RED NO. 40

Listerine Clinical Solutions Gum Health Icy Mint

Drug Facts

Active ingredients

Eucalyptol 0.092%,
Menthol 0.042%,
Methyl Salicylate 0.060%,
Thymol 0.064%

Purposes

Antiplaque/antigingivitis

Uses

helps prevent and reduce:

• plaque

• gingivitis

Warnings

Do not use in children under 12 years of age

ASK DOCTOR

Ask a dentist if symptoms persist, new symptoms appear, or conditions worsen after regular use

Keep out of reach of children. If more than used for rinsing is accidentally swallowed, get medical help or contact a Poison Control Center right away.

Directions

• rinse full strength for 30 seconds with 20 mL (2/3 fluid ounce or 4 teaspoonfuls) morning and night

• do not swallow

Other information

• this rinse is not intended to replace brushing or flossing

• store at room temperature

• cold weather may cloud this product. Its antiseptic properties are not affected.

Inactive ingredients

Water, Alcohol (21.6% v/v), Sorbitol, Poloxamer 407, Flavor, Zinc Chloride, Benzoic Acid, Sodium Benzoate, Sodium Saccharin, Sucralose, Red 40

Questions?

call toll-free 888-222-0182 or 215-273-8755 (collect)

Distributed by:
JOHNSON & JOHNSON CONSUMER INC.
Skillman, NJ 08558

PRINCIPAL DISPLAY PANEL - 1 L Bottle Label

ANTIGINGIVITIS / ANTIPLAQUE MOUTHWASH

LISTERINE®

CLINICAL

SOLUTIONS^+

ANTISEPTIC

GUM HEALTH

Powered with Zinc to reduce build up and kills 99.9%

of the germs that cause bleeding and inflammation

(*vs brushing alone)

ICY MINT

1.0 L (1 Qt 1.8 Fl Oz)